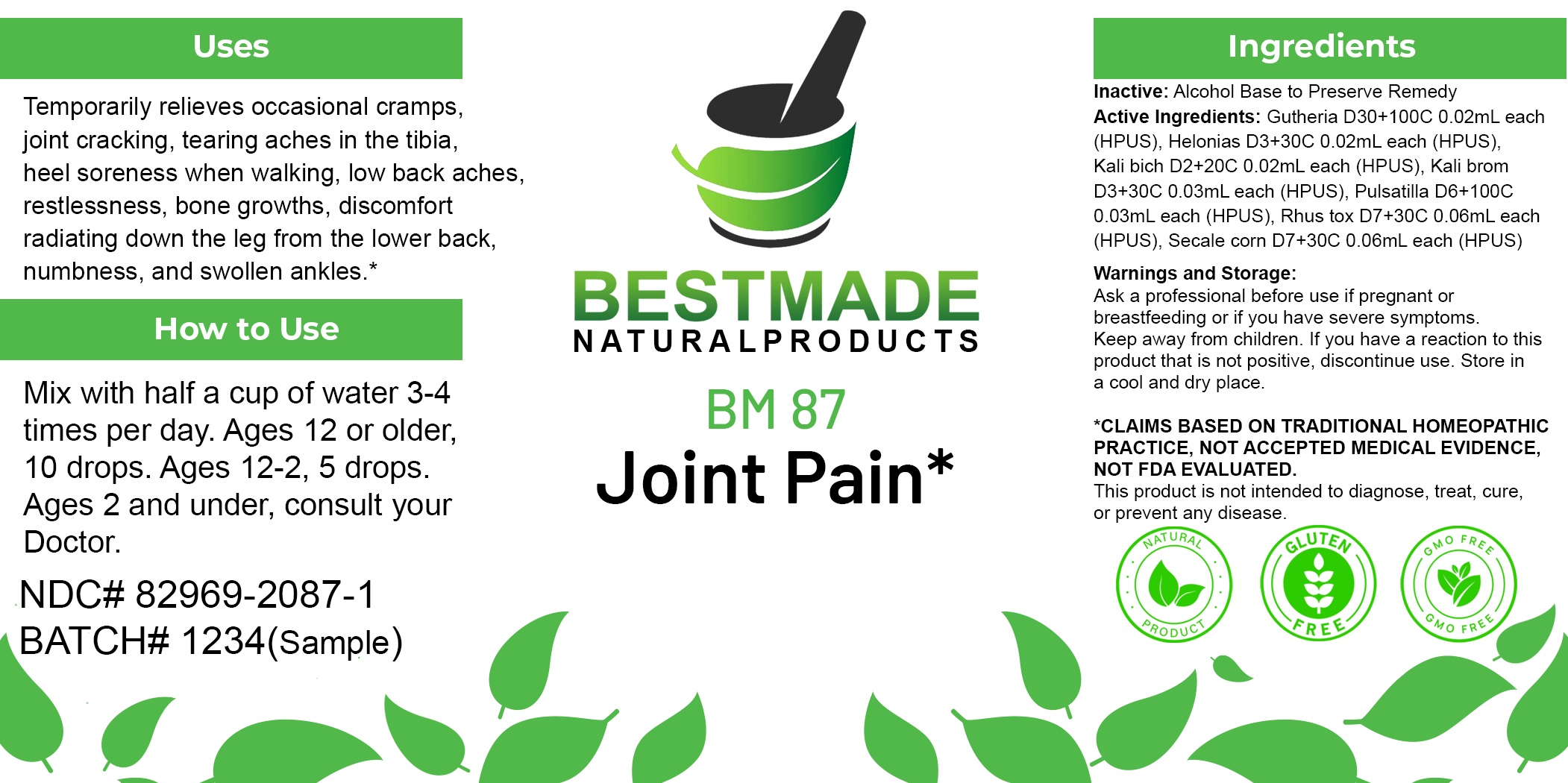 DRUG LABEL: Bestmade Natural Products BM87
NDC: 82969-2087 | Form: LIQUID
Manufacturer: Bestmade Natural Products
Category: homeopathic | Type: HUMAN OTC DRUG LABEL
Date: 20250203

ACTIVE INGREDIENTS: GAULTHERIA PROCUMBENS TOP 30 [hp_C]/30 [hp_C]; CHAMAELIRIUM LUTEUM ROOT 30 [hp_C]/30 [hp_C]; TOXICODENDRON PUBESCENS LEAF 30 [hp_C]/30 [hp_C]; PULSATILLA PRATENSIS 30 [hp_C]/30 [hp_C]; POTASSIUM BROMIDE 30 [hp_C]/30 [hp_C]; POTASSIUM DICHROMATE 30 [hp_C]/30 [hp_C]; CLAVICEPS PURPUREA SCLEROTIUM 30 [hp_C]/30 [hp_C]
INACTIVE INGREDIENTS: ALCOHOL 30 [hp_C]/30 [hp_C]

BM87

DOSAGE AND ADMINISTRATION

How to Use

Mix with half a cup of water 3-4 times per day. Ages 12 or older, 10 drops. Ages 12-2, 5 drops. Ages 2 and under, consult your Doctor.

INACTIVE INGREDIENT

Ingredients

Inactive: Alcohol Base to Preserve Remedy

ACTIVE INGREDIENT

Active Ingredients: Gutheria D30+100C 0.02mL each (HPUS), Helonias D3+30C 0.02mL each (HPUS), Kali bich D2+20C 0.02mL each (HPUS), Kali brom D3+30C 0.03mL each (HPUS), Pulsatilla D6+100C 0.03mL each (HPUS), Rhus tox D7+30C 0.06mL each (HPUS), Secale corn D7+30C 0.06mL each (HPUS).

Uses

Temporarily relieves occasional cramps, joint cracking, tearing aches in the tibia, heel soreness when walking, low back aches, restlessness, bone growths, discomfort radiating down the leg from the lower back, numbness, and swollen ankles.*

*CLAIMS BASED ON TRADITIONAL HOMEOPATHIC PRACTICE, NOT ACCEPTED MEDICAL EVIDENCE, NOT FDA EVALUATED.

This product is not intended to diagnose, treat, cure, or prevent any disease.

Uses

Temporarily relieves occasional cramps, joint cracking, tearing aches in the tibia, heel soreness when walking, low back aches, restlessness, bone growths, discomfort radiating down the leg from the lower back, numbness, and swollen ankles.*

*CLAIMS BASED ON TRADITIONAL HOMEOPATHIC PRACTICE, NOT ACCEPTED MEDICAL EVIDENCE, NOT FDA EVALUATED.

This product is not intended to diagnose, treat, cure, or prevent any disease.

KEEP OUT OF REACH OF CHILDREN

Warnings and Storage:

Ask a professional before use if pregnant or breastfeeding or if you have severe symptoms. Keep away from children. If you have a reaction to this product that is not positive, discontinue use. Store in a cool and dry place.

Warnings and Storage:

Ask a professional before use if pregnant or breastfeeding or if you have severe symptoms. Keep away from children. If you have a reaction to this product that is not positive, discontinue use. Store in a cool and dry place.

*CLAIMS BASED ON TRADITIONAL HOMEOPATHIC PRACTICE, NOT ACCEPTED MEDICAL EVIDENCE, NOT FDA EVALUATED. This product is not intended to diagnose, treat, cure, or prevent any disease.

Entire package label